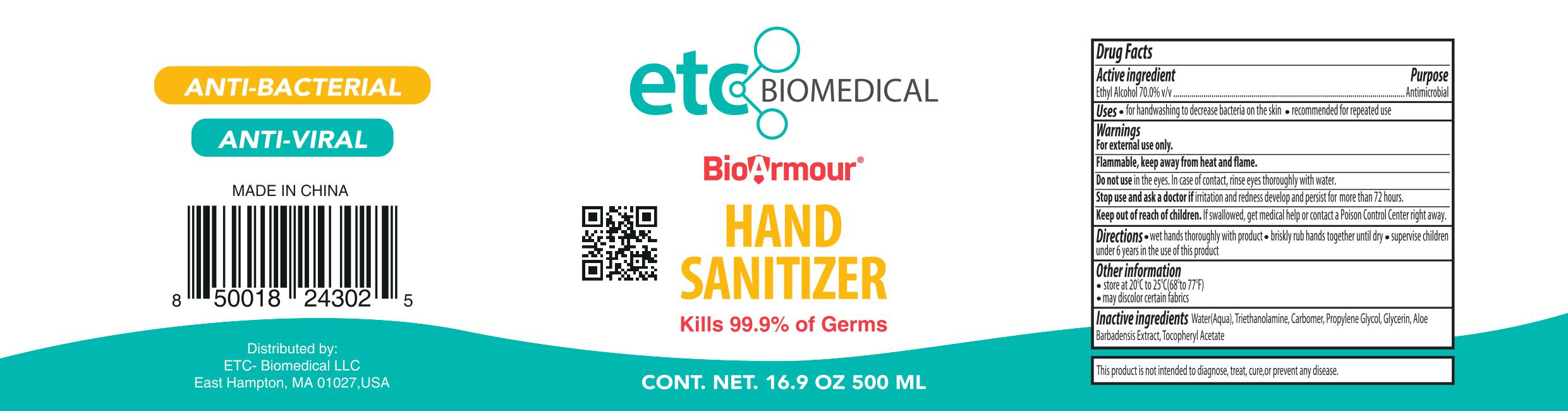 DRUG LABEL: BioArmour Hand Sanitizer
NDC: 75749-001 | Form: GEL
Manufacturer: Ningbo Pretty Tourism Manufacturer Co. Ltd.
Category: otc | Type: HUMAN OTC DRUG LABEL
Date: 20200511

ACTIVE INGREDIENTS: ALCOHOL 70 mL/100 mL
INACTIVE INGREDIENTS: TROLAMINE; PROPYLENE GLYCOL; ALOE VERA LEAF; GLYCERIN; WATER; ALPHA-TOCOPHEROL ACETATE; CARBOMER HOMOPOLYMER, UNSPECIFIED TYPE

BioArmour Hand Sanitizer (Squeeze hose)

Active Ingredient(s)

Ethyl Alcohol 70% Purpose: Antimicrobial

Purpose

Antimicrobial

Uses

Use(s)

- For handwashing to decrease bacteria on the skin
- Recommended for repeated use

Warnings

For external use only. Flammable, keep away from heat and flame.

Do not use in the eyes. In case of contact, rinse eyes thoroughly with water.

- Stop use and ask a doctor if irritation and redness develop and persist for more than 72 hours.

Keep out of reach of children. If swallowed, get medical help or contact a Poison Control Center right away.

Directions

- Wet hands thoroughly with product
- Briskly rub hands together until dry
- Supervise children under 6 years in the use of this product

Other information

- Store at 20oC to 25oC (68o to 77oF)
- May discolor certain fabrics

Inactive ingredients

Water (aqua), Triethanolamine, Carbomer, Propylene Glycol, Glycerin, Aloe Barbadensis Extract, Tocopheryl Acetate